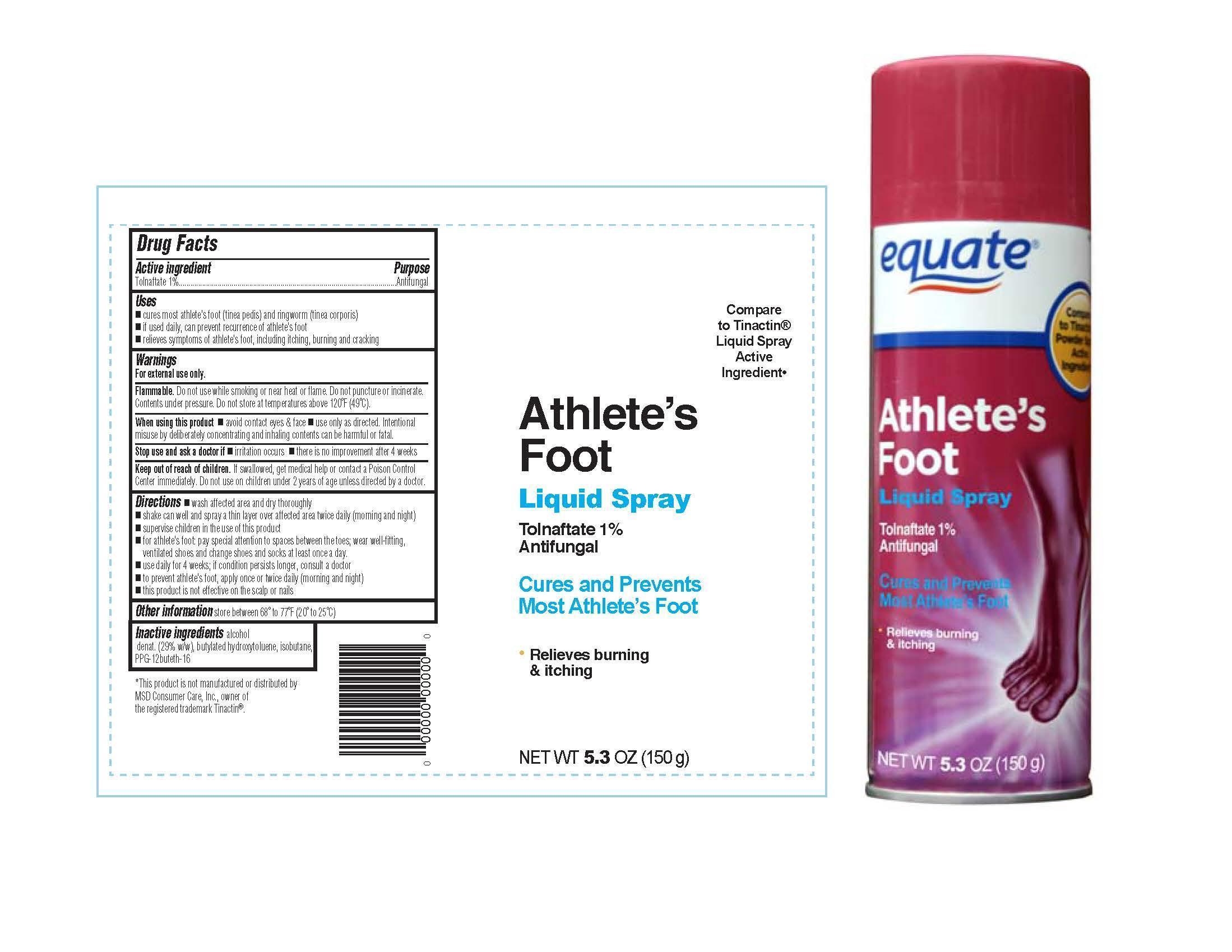 DRUG LABEL: Equate Liquid Foot
NDC: 50942-002 | Form: SPRAY
Manufacturer: Zhejiang Ludao Cosmetics Co., Ltd.
Category: otc | Type: HUMAN OTC DRUG LABEL
Date: 20181220

ACTIVE INGREDIENTS: TOLNAFTATE 1 g/150 g
INACTIVE INGREDIENTS: ALCOHOL; BUTYLATED HYDROXYTOLUENE; ISOBUTANE; PPG-12-BUTETH-16

Equate Antifungal

Active Ingredient ............................................ Purpose

Tolnaftate 1% .................................................. Antifungal

Uses

- cures most athlete's foot (tinea pedis) and ringworm (tinea corporis)
- if used daily, can prevent recurrence of athlete's foot
- relieves symptoms of athlete's foot, including itching, burning and cracking

Keep out of reach of children. If swallowed, get medical help or contact a Poison Control Center immediately. Do not use on children under 2 years of age unless directed by a doctor.

INDICATIONS AND USAGE

Athlete's Food

Liquid Spray

Tolnaftate 1%

Cures and Prevents Most Athlete's Foot

Relieves burning and itching

Net Wt 5.3 OZ (150 g)

Warnings

For external use only.

Flammable. Do not use while smoking or near heat or flame. Do not puncture or incinerate. Contents under pressure. Do not store at temperatures above 120oF (49oC).

When using this product

- avoid eyes & face
- use only as directed. Intentional misuse by deliberately concentrating and inhaling contents can be harmful or fatal.

Stop use and ask a doctor if

- irritation occurs
- there is no improvement after 4 weeks

Directions

- wash affected area and dry thoroughly
- shake can well and spray a thin layer over affected area twice daily (morning and night)
- supervise children in the use of this product
- for athlete's foot: pay special attention to spaces betwen the toes; wear well-fitted, ventilated shoes and change shoes and socks at least once a day.
- use daily for 4 weeks; if condition persists longer, consult a doctor
- to prevent athlete's foot, apply once or twice daily (morning and night)
- in case of clogging, clean nozzle with a pin

Inactive Ingredients

alcohol denat. (29% w/w), butylated hydroxytoluene, isobutane, PPG-12buteth-16

Other information store between 68o to 77oF (20o to 25oC)

*This product is not manufactured or distributed by MSF Consumer Care, Inc., owner of the registered trademark Tinactin(R).